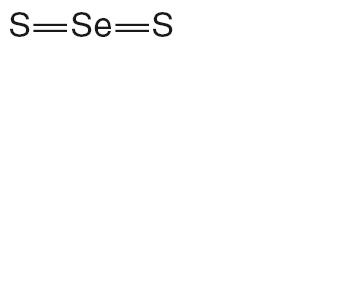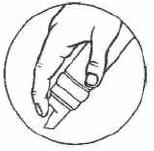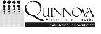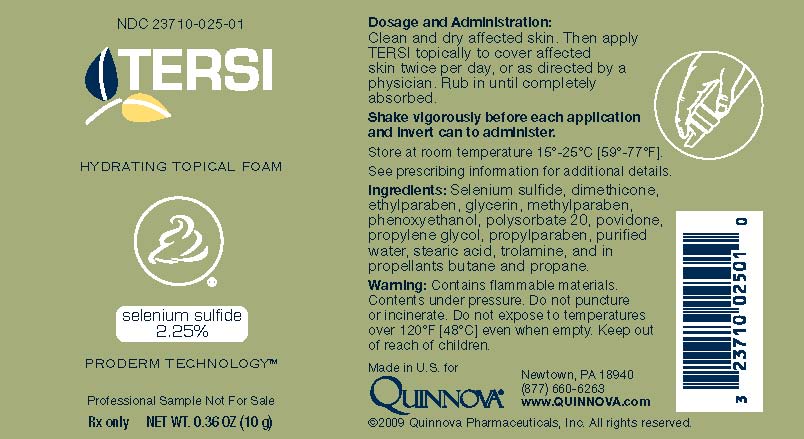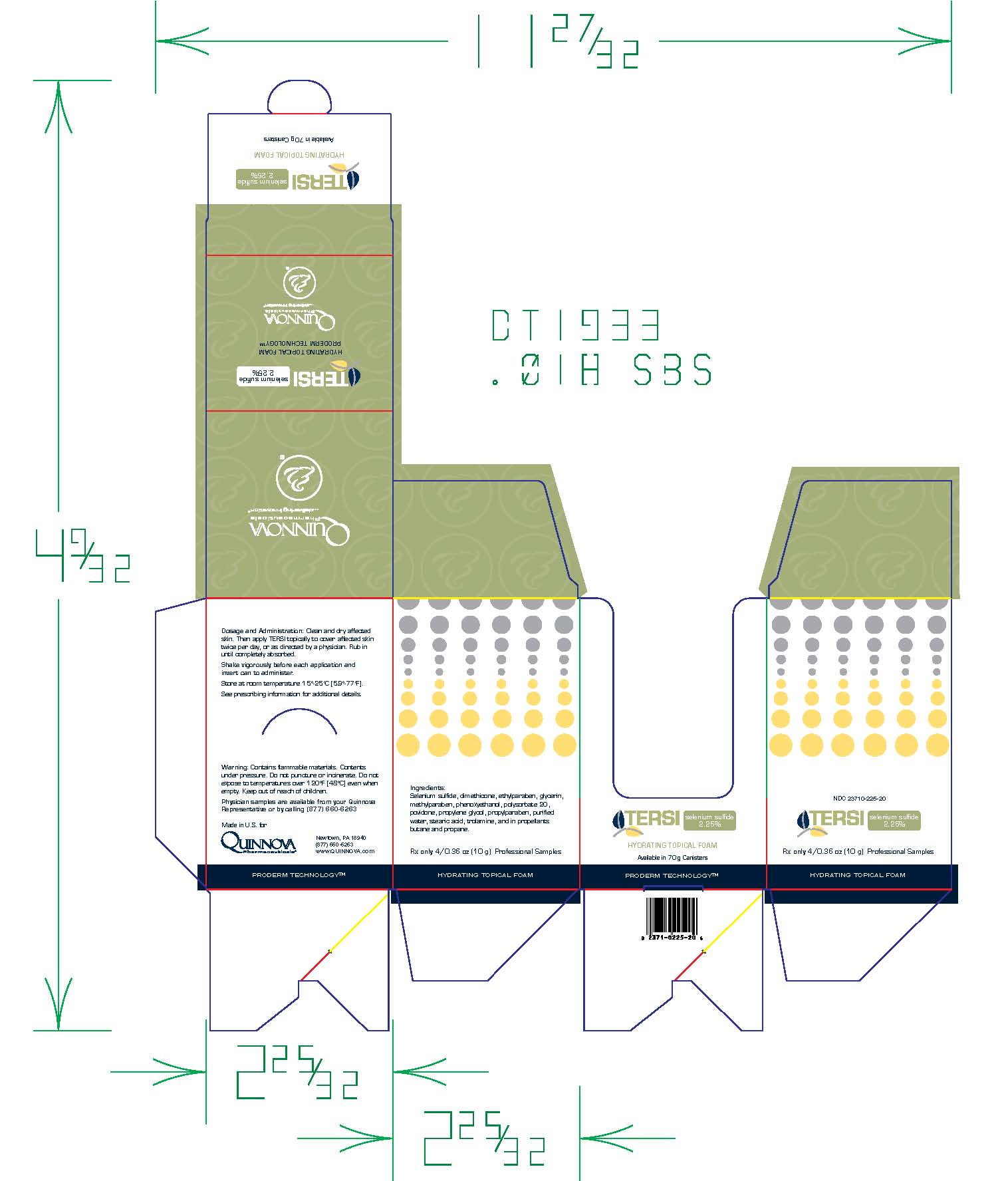 DRUG LABEL: TERSI
NDC: 23710-225 | Form: AEROSOL, FOAM
Manufacturer: Quinnova Pharmaceuticals, Inc.
Category: other | Type: NON-STANDARDIZED ALLERGENIC LABEL
Date: 20091204

ACTIVE INGREDIENTS: SELENIUM SULFIDE 1.44 g/70 g
INACTIVE INGREDIENTS: POVIDONE K29/32; STEARIC ACID; PROPYLENE GLYCOL; GLYCERIN; DIMETHICONE; POLYSORBATE 20; ETHYLPARABEN; PROPYLPARABEN; PHENOXYETHANOL; METHYLPARABEN; WATER; TROLAMINE

TERSI

TERSI Hydrating Topical Foam

(selenium sulfide in a water and lipid based foam, 2.25%)

Rx Only

DESCRIPTION

TERSI, which is applied topically, is an antiseborrheic, antifungal preparation for the treatment of seborrheic dermatitis and tinea versicolor of the skin. Each gram of TERSI contains selenium sulfide 2.25% as the active ingredient, and the following inactive ingredients: dimethicone, ethylparaben, glycerin, methylparaben, phenoxyethanol, polysorbate 20, povidone, propylene glycol, propylparaben, purified water, stearic acid, trolamine, and in propellants butane and propane.

CHEMICAL STRUCTURE

Selenium sulfide has the following chemical structure:

CLINICAL PHARMACOLOGY

Topically applied selenium sulfide appears to have a cytostatic effect on cells of the epidermis, reducing corneocyte production.

PHARMACOKINETICS

The mechanism of action of topically applied selenium sulfide is not yet known.

INDICATIONS AND USAGE

For the treatment of seborrheic dermatitis and tinea versicolor of the skin.

CONTRAINDICATIONS

Known hypersensitivity to any of the listed ingredients.

WARNINGS

TERSI is for external use only. It is not for ophthalmic, oral, anal or intravaginal use. Contact with eyes, lips, broken or inflamed skin, and all mucous membranes should be avoided. TERSI should not be used by persons who have a known hypersensitivity to selenium sulfide or any of the other listed ingredients.

PRECAUTIONS

TERSI should be used only as directed by a physician and should not be used to treat any condition other than that for which it is prescribed.TERSI should not be used on any skin area where inflammation or exudation is present as increased absorption may occur. If redness or irritation occurs, discontinue use and consult with prescribing physician.

Pregnancy (Category C)

Animal reproduction studies have not been performed with topically applied selenium sulfide and it is not known whether TERSI can cause fetal harm when administered to a pregnant woman. Nevertheless, TERSI should be used by a pregnant woman only if necessary.

Nursing Mothers

It is not known whether topically applied selenium sulfide is excreted in human milk. Due to the fact that many drugs are excreted in human milk, caution should be exercised by physicians when administering TERSI to nursing mothers.
KEEP THIS AND ALL OTHER MEDICATIONS OUT OF THE REACH OF CHILDREN.

ADVERSE REACTIONS

Transient stinging, burning, itching or irritation is possible.

DOSAGE AND ADMINISTRATION

Unless otherwise directed by a prescribing physician,TERSI should be applied to affected area twice a day.TERSI should be rubbed into the skin until it is completely absorbed.

TERSI should be shaken vigorously before each application and inverted to administer.

HOW SUPPLIED

TERSI is supplied in a 70 gram or 2.5 ounce aerosolized canister bearing the NDC Number 23710-225-70 and a 10 gram or 0.36 ounce aerosolized canister bearing the NDC Number 23710-025-01. The 10 gram canister is physician dispensed sample product.

Store at controlled room temperature 15º - 25ºC (59º - 77ºF).

Contains flammable materials. Contents under pressure. Do not puncture or incinerate. Do not expose to temperatures over 120ºF [48ºC] even when empty. Keep out of reach of children.

TERSI is covered by U.S. Patent 5,993,830.

TERSI is manufactured for Quinnova Pharmaceuticals, Inc., Newtown, PA 18940, (877) 6606263, www.QUINNOVA.com.

Prescribing Information as of September2007.

TRSFO025 7/08